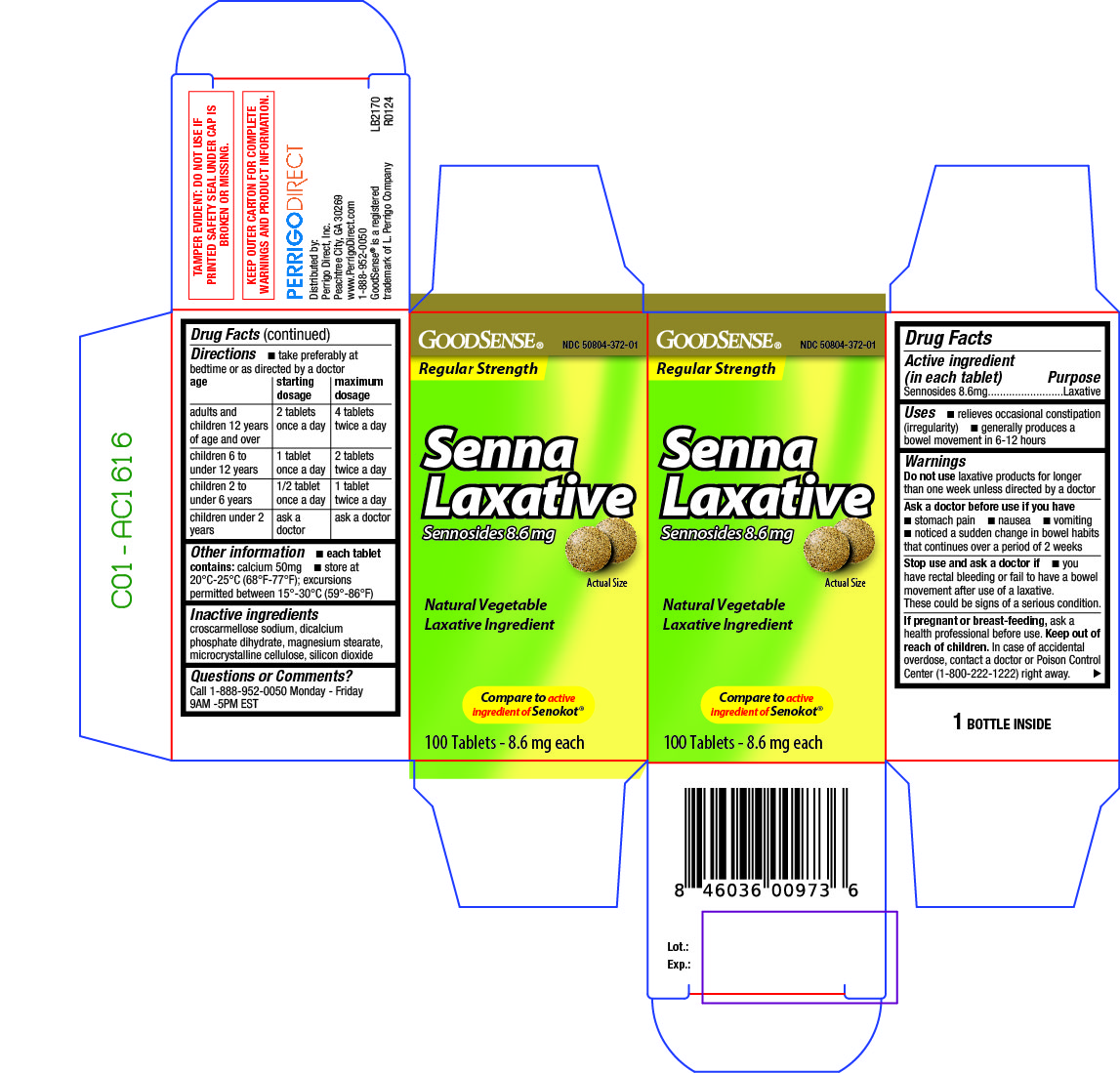 DRUG LABEL: Senna Laxative
NDC: 50804-372 | Form: TABLET
Manufacturer: Good Sense
Category: otc | Type: HUMAN OTC DRUG LABEL
Date: 20240618

ACTIVE INGREDIENTS: SENNOSIDES 8.6 mg/1 1
INACTIVE INGREDIENTS: CROSCARMELLOSE SODIUM; DIBASIC CALCIUM PHOSPHATE DIHYDRATE; MAGNESIUM STEARATE; MICROCRYSTALLINE CELLULOSE; SILICON DIOXIDE

371 - Senna Laxative

Active ingredient(s)

Sennosides 8.6mg

Purpose

Laxative

Use(s)

- relieves occasional constipation (irregularity)
- generally produces a bowel movement in 6-12 hours

Warnings

Do not use

laxative products for longer than one week unless directed by a doctor

Ask a doctor before use if

- stomach pain
- nausea
- vomiting
- noticed a sudden change in bowel habits that continues over a period of 2 weeks

Stop use and ask a doctor if

you have rectal bleeding or fail to have a bowel movement after use of a laxative. These could be signs of a serious condition.

If pregnant or breastfeeding,

ask a health professional before use.

Keep out of reach of children

In case of accidental overdose, contact a doctor or Poison Control Center (1-800-222-1222) right away.

Directions

- Take preferably at bedtime or as directed by a doctor

Age | Starting Dosage | Maximum Dosage
adults and children 12 years of age and over | 2 tablets once a day | 4 tablets twice a day
children 6 to under 12 years | 1 tablet once a day | 2 tablets twice a day
children 2 to under 6 years | 1/2 tablet once a day | 1 tablet twice a day
children under 2 years | ask a doctor | ask a doctor

Other information

- each tablet contains: calcium 50mg
- store at 20°C-25°C (68°F-77°F); excursions permitted between 15°-30°C (59°-86°F)
- do not use if safety seal under cap is broken or missing

Inactive ingredients

croscarmellose sodium, dibasic calcium phosphate, magnesium stearate, microcrystalline cellulose, silicon dioxide

Questions/Comments

Call 1-888-952-0050 Monday - Friday 9AM -5PM EST,

Principal Display Panel

Senna Laxative